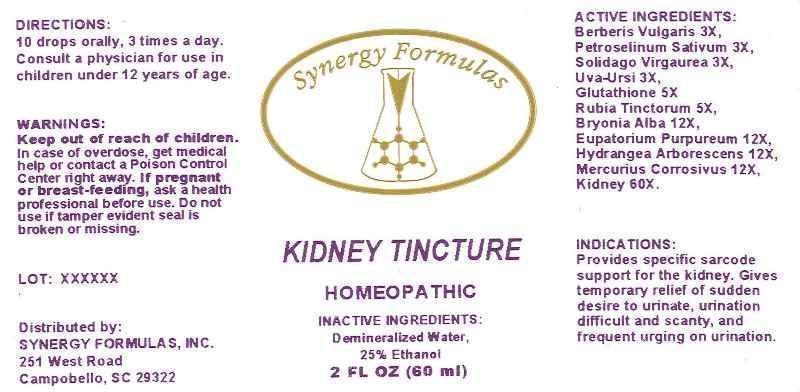 DRUG LABEL: Kidney Tincture
NDC: 43772-0022 | Form: LIQUID
Manufacturer: Synergy Formulas, Inc.
Category: homeopathic | Type: HUMAN OTC DRUG LABEL
Date: 20140102

ACTIVE INGREDIENTS: BERBERIS VULGARIS ROOT BARK 3 [hp_X]/1 mL; PETROSELINUM CRISPUM 3 [hp_X]/1 mL; SOLIDAGO VIRGAUREA FLOWERING TOP 3 [hp_X]/1 mL; ARCTOSTAPHYLOS UVA-URSI LEAF 3 [hp_X]/1 mL; GLUTATHIONE 5 [hp_X]/1 mL; RUBIA TINCTORUM ROOT 5 [hp_X]/1 mL; BRYONIA ALBA ROOT 12 [hp_X]/1 mL; EUPATORIUM PURPUREUM ROOT 12 [hp_X]/1 mL; HYDRANGEA ARBORESCENS ROOT 12 [hp_X]/1 mL; MERCURIC CHLORIDE 12 [hp_X]/1 mL; PORK KIDNEY 60 [hp_X]/1 mL
INACTIVE INGREDIENTS: WATER; ALCOHOL

DRUG FACTS:

ACTIVE INGREDIENTS:

Berberis Vulgaris 3X, Petroselinum Sativum 3X, Solidago Virgaurea 3X, Uva-Ursi 3X, Glutathione 5X, Rubia Tinctorum 5X, Bryonia (Alba) 12X, Eupatorium Purpureum 12X, Hydrangea Arborescens 12X, Mervurius Corrosivus 12X, Kidney (Suis) 60X

INDICATIONS:

Provides specific sarcode support for the kidney. Gives temporary relief of sudden desire to urinate, urination difficult and scanty, and frequent urging on urination.

WARNINGS:

Keep out of reach of children. In case of overdose, get medical help or contact a Poison Control Center right away.

If pregnant or breast-feeding, ask a health professional before use.

Do not use if tamper evident seal is broken or missing.

Keep out of reach of children. In case of overdose, get medical help or contact a Poison Control Center right away.

DIRECTIONS:

10 drops orally, 3 times a day. Consult a physician for use in children under 12 years of age.

INDICATIONS:

Provides specific sarcode support for the kidney. Gives temporary relief of sudden desire to urinate, urination difficult and scanty, and frequent urging on urination.

INACTIVE INGREDIENTS:

Demineralized Water, 25% Ethanol

QUESTIONS:

Distributed by:

SYNERGY FORMULAS, INC.

251 West Road

Campobello, SC 29322

PACKAGE DISPLAY LABEL:

Synergy Formulas

KIDNEY TINCTURE

HOMEOPATHIC

2 FL OZ (60 ml)